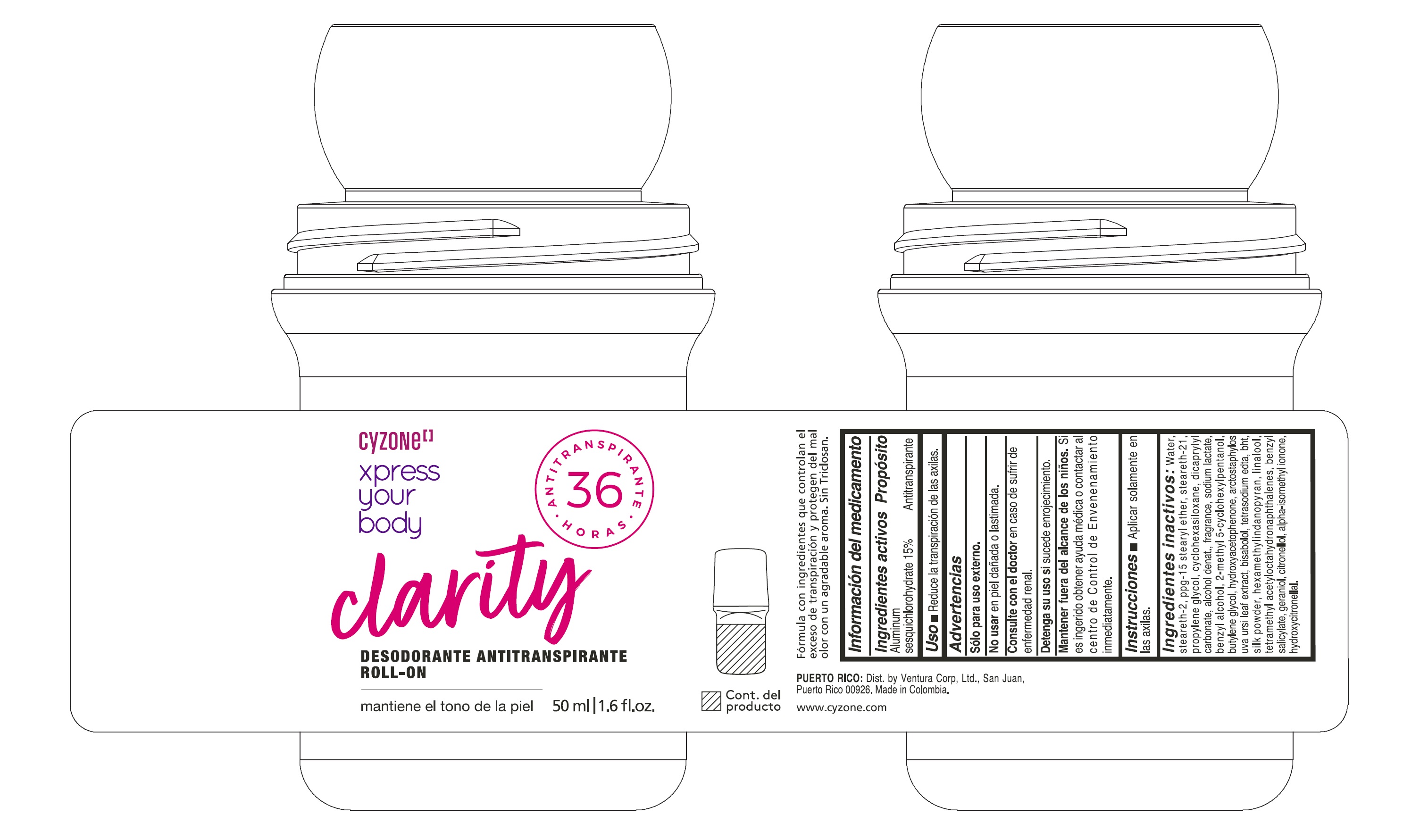 DRUG LABEL: CYZONE XPRESS YOUR BODY CLARITY DESODORANTE ANTITRANSPIRANTE ROLL ON
NDC: 14141-466 | Form: EMULSION
Manufacturer: BEL STAR S A
Category: otc | Type: HUMAN OTC DRUG LABEL
Date: 20260226

ACTIVE INGREDIENTS: ALUMINUM SESQUICHLOROHYDRATE 150 mg/1 mL
INACTIVE INGREDIENTS: WATER; GERANIOL; DICAPRYLYL CARBONATE; TETRAMETHYL ACETYLOCTAHYDRONAPHTHALENES; BENZYL SALICYLATE; BISABOLOL; CYCLOHEXASILOXANE; ALCOHOL; BENZYL ALCOHOL; TETRASODIUM EDTA; BHT; HEXAMETHYLINDANOPYRAN; LINALOOL, (+)-; ALPHA-ISOMETHYL IONONE; HYDROXYCITRONELLAL; PPG-15 STEARYL ETHER; STEARETH-21; BUTYLENE GLYCOL; PROPYLENE GLYCOL; STEARETH-2; SODIUM LACTATE; HYDROXYACETOPHENONE; CITRONELLOL; 2-METHYL 5-CYCLOHEXYLPENTANOL; ARCTOSTAPHYLOS UVA-URSI LEAF

CYZONE XPRESS YOUR BODY CLARITY DESODORANTE ANTITRANSPIRANTE ROLL ON

Ingredientes activos

Aluminum Sesquichlorohydrate 15%

Propósito

Antitranspirante

Uso

Reduce la transpiración de las axilas

Advertencias

Sólo para uso externo.

No usar

en piel dañada o lastimada

Consulte con el doctor

en caso de sufrir de enfermedad renal

Detenga su uso si

sucede enrojecimiento

Mantener fuera del alcance de los niños.

Si es ingerido obtener ayuda médica o contactar al centro de Control de Envenenamiento inmediatamente

Instrucciones

Aplicar solamente en las axilas.

Ingredientes inactivos

Water, steareth-2, ppg-15 stearyl ether, steareth-21, propylene glycol, cyclohexasiloxane, dicaprylyl carbonate, alcohol denat., fragrance, sodium lactate, benzyl alcohol, 2-methyl 5-cyclohexylpentanol, butylene glycol, hydroxyacetophenone, arctostaphylos uva ursi leaf extract, bisabolol, tetrasodium edta, bht, silk powder, hexamethylindanopyran, linalool, tetramethyl acetyloctahydronaphthalenes, benzyl salicylate, geraniol, citronellol, alpha-isomethyl ionone, hydroxycitronellal.